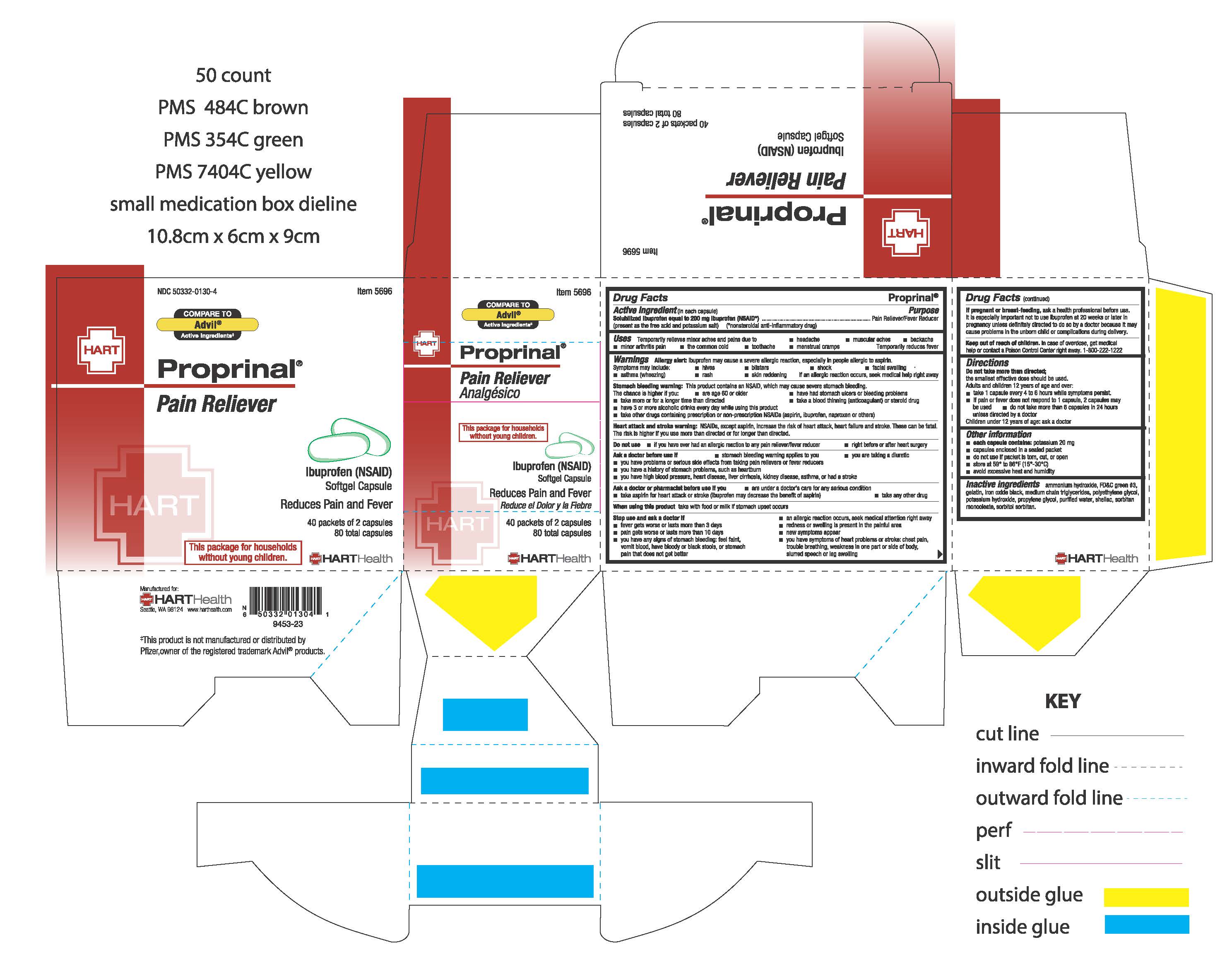 DRUG LABEL: PROPRINAL
NDC: 50332-0130 | Form: CAPSULE, LIQUID FILLED
Manufacturer: HART Health
Category: otc | Type: HUMAN OTC DRUG LABEL
Date: 20241204

ACTIVE INGREDIENTS: IBUPROFEN 200 mg/1 1
INACTIVE INGREDIENTS: WATER; SHELLAC; FD&C GREEN NO. 3; AMMONIA; GELATIN; FERROSOFERRIC OXIDE; POLYETHYLENE GLYCOL, UNSPECIFIED; MEDIUM-CHAIN TRIGLYCERIDES; PROPYLENE GLYCOL; POTASSIUM HYDROXIDE; SORBITAN MONOOLEATE; SORBITOL

PROPRINAL

Active ingredient (in each capsule)
Solubilized Ibuprofen equal to
200 mg ibuprofen (NSAID)*
(present as the free acid and potassium salt)
* nonsteroidal anti-inflammatory drug

Purpose
Pain reliever/Fever reducer

Uses:

Temporarily relieves minor aches and pains due to:

- headache
- muscular aches
- backache
- minor arthritis pain
- the common cold
- toothache
- menstrual cramps

Temporarily reduces fever

Warnings
Allergy alert: Ibuprofen may cause a severe allergic reaction, especially in people allergic to aspirin. Symptoms may include:

- hives
- blisters
- shock
- facial swelling
- asthma (wheezing)
- rash
- skin reddening

If an allergic reaction occurs, stop use and seek medical help right away.

Stomach bleeding warning: This product contains an NSAID, which may cause severe stomach bleeding. The chance is higher if you:

- are age 60 or older
- have had stomach ulcers or bleeding problems
- take a blood thinning (anticoagulant) or steroid drug
- take other drugs containing prescription or nonprescription NSAIDs (aspirin, ibuprofen, naproxen or others)
- have 3 or more alcoholic drinks every day while using this product
- take more or for a longer time than directed

Heart attack and stroke warning: NSAIDs, except aspirin, increase the risk of heart attack, heart failure and stroke. These can be fatal. The risk is higher if you use more than directed or for longer than directed.

Do not use

- if you have ever had an allergic reaction to any pain reliever/fever reducer
- right before or after heart surgery

Ask a doctor before use if

- stomach bleeding warning applies to you
- you have problems or serious side effects from taking pain relievers or fever reducers
- you have a history of stomach problems, such as heartburn
- you have high blood pressure, heart disease, liver cirrhosis, kidney disease, asthma, or had a stroke
- you are taking a diuretic

Ask a doctor or pharmacist before use if you

- are under a doctor's care for any serious condition
- take aspirin for heart attack or stroke (ibuprofen may decrease this benefit of aspirin)
- take any other drug

WHEN USING

When using this produc take with food or milk if stomach upset occurs

Stop use and ask a doctor if

- an allergic reaction occurs, seek medical help right away
- fever worsens or lasts more than 3 days
- pain worsens or lasts more than 10 days
- you have any of the following signs of stomach bleeding: feel faint, vomit blood, have bloody or black stools, or stomach pain that does not get better
- new symptoms occur
- redness or swelling is present
- you have symptoms of heart problems or stroke: chest pain, trouble breathing, weakness in one part or side of the body, slurred speech, or leg swelling

PREGNANCY OR BREAST FEEDING

If pregnant or breast-feeding, ask a health professional before use. It is especially important not to use ibuprofen at 20 weeks or later in pregnancy unless definitely directed to do so by a doctor because it may cause problems in the unborn child or complications during delivery.

Keep out of reach of children. In case of overdose, get medical help or contact a Poison Control Center right away (1-800-222-1222).

Directions

do not take more than directed

the smallest effective dose should be used

adults and children 12 years and over:

- take 1 capsule every 4 to 6 hours while symptoms persist
- if pain or fever does not respond to 1 capsule, 2 capsules may be used
- do not take more than 6 capsules in 24 hours, unless directed by a doctor

children under 12 years of age : ask a doctor

OTHER INFORMATION

- each capsule contains: potassium 20 mg
- caplets enclosed in a sealed packet
- do not use if packet is torn, cut or open
- store at 59° to 86°F (15°-30°C)
- avoid excessive heat and humidity

INACTIVE INGREDIENT

Inactive ingredients Ammonium hydroxide, FD&C green #3, gelatin, iron oxide black, medium chain triglycerides, polyethylene glycol, propylene glycol, potassium hydroxide, purified water, shellac, sorbitan monooleate, sorbitol sorbitan